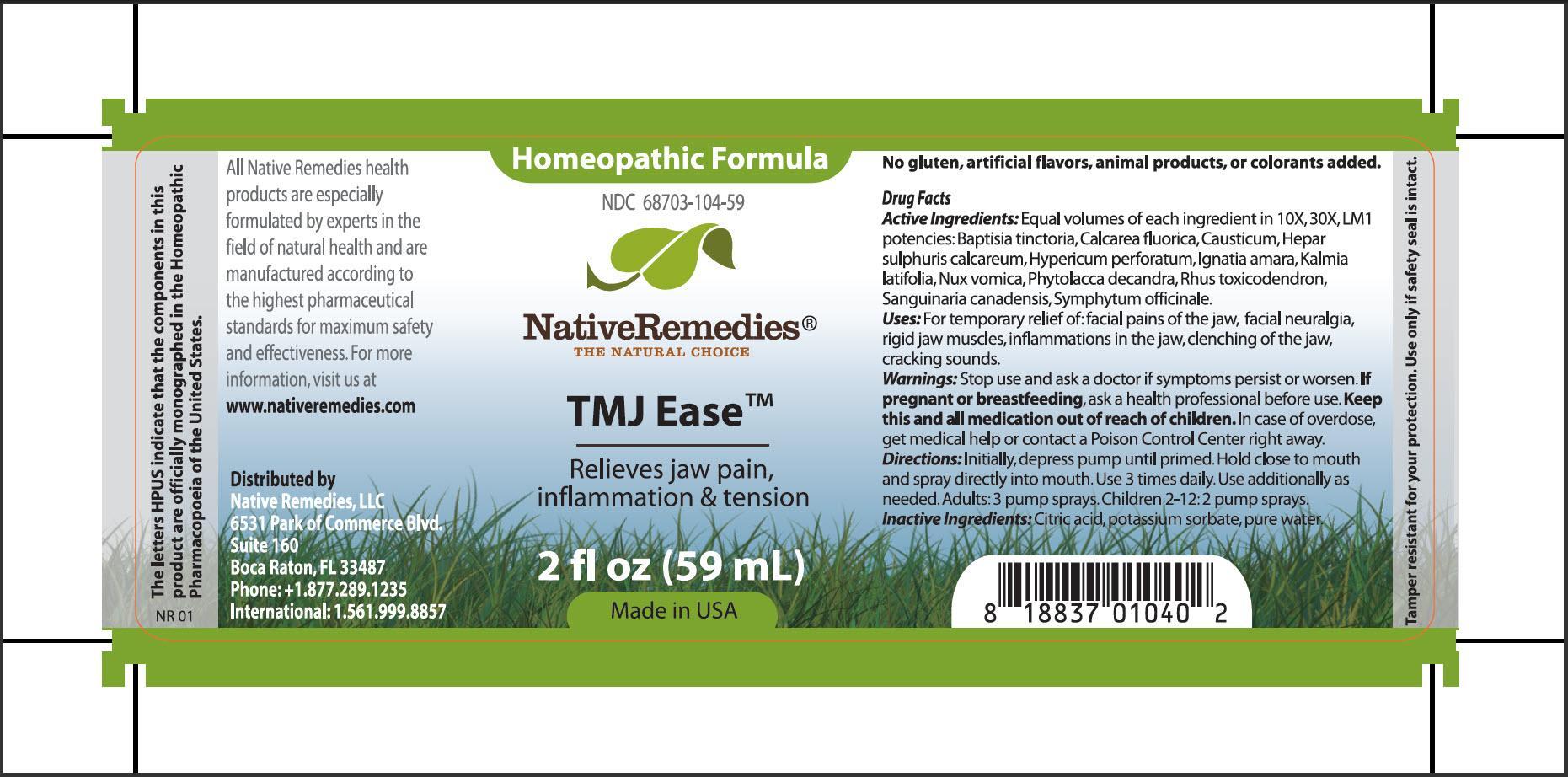 DRUG LABEL: TMJ Ease
NDC: 68703-104 | Form: SPRAY
Manufacturer: Native Remedies, LLC
Category: homeopathic | Type: HUMAN OTC DRUG LABEL
Date: 20130627

ACTIVE INGREDIENTS: BAPTISIA TINCTORIA ROOT 10 [hp_X]/59 mL; CALCIUM FLUORIDE 10 [hp_X]/59 mL; CAUSTICUM 10 [hp_X]/59 mL; CALCIUM SULFIDE 10 [hp_X]/59 mL; HYPERICUM PERFORATUM 10 1/59 mL; STRYCHNOS IGNATII SEED 10 [hp_X]/59 mL; KALMIA LATIFOLIA LEAF 10 [hp_X]/59 mL; STRYCHNOS NUX-VOMICA SEED 10 [hp_X]/59 mL; PHYTOLACCA AMERICANA ROOT 10 [hp_X]/59 mL; TOXICODENDRON PUBESCENS LEAF  10 [hp_X]/59 mL; SANGUINARIA CANADENSIS ROOT 10 [hp_X]/59 mL; COMFREY ROOT 10 [hp_X]/59 mL
INACTIVE INGREDIENTS: CITRIC ACID MONOHYDRATE; POTASSIUM SORBATE; WATER

TMJ Ease

PURPOSE

Relieves jaw pain, inflammation and tension

Drug Facts
Active Ingredients: Equal volumes of each ingredient in 10X, 30X, LM1 potencies: Baptisia tinctoria, Calcarea fluorica, Causticum, Hepar sulphuris calcareum, Hypericum perforatum, Ignatia amara, Kalmia latifolia, Nux vomica, Phytolacca decandra, Rhus toxicodendron, Sanguinaria canadensis, Symphytum officinale

INDICATIONS AND USAGE

Uses: For temporary relief of: facial pains of the jaw, facial neuralgia, rigid jaw muscles, inflammations in the jaw, clenching of the jaw, cracking sounds

WARNINGS

Warnings: Stop use and ask a doctor if symptoms persist or worsen

PREGNANCY OR BREAST FEEDING

If pregnant or breastfeeding, ask a health professional before use

KEEP OUT OF REACH OF CHILDREN

Keep this and all medication out of reach of children

OVERDOSAGE

In case of overdose, get medical help or contact a Poison Control Center right away

DOSAGE AND ADMINISTRATION

Directions: Initially, depress pump until primed. Hold close to mouth and spray directly into mouth. Use 3 times daily. Use additionally as needed. Adults: 3 pumps sprays. Children 2-12: 2 pump sprays

Inactive Ingredients: Citric acid, potassium sorbate, pure water

PATIENT COUNSELING INFORMATION

The letters HPUS indicate that the components in this product are officially monographed in the Homeopathic Pharmacopoeia of the United States

All Native Remedies health products are especially formulated by experts in the field of natural health and are manufactured according to the highest pharmaceutical standards for maximum safety and effectiveness. For more information, visit us at www.nativeremedies.com

Distributed by
Native Remedies, LLC
6531 Park of Commerce Blvd.
Suite 160
Boca Raton, FL 33487
Phone: +1.877.289.1235
International: 1.561.999.8857

No gluten, artificial flavors, animal products, or colorants added

STORAGE AND HANDLING

Tamper resistant for your protection. Use only if safety seal is intact